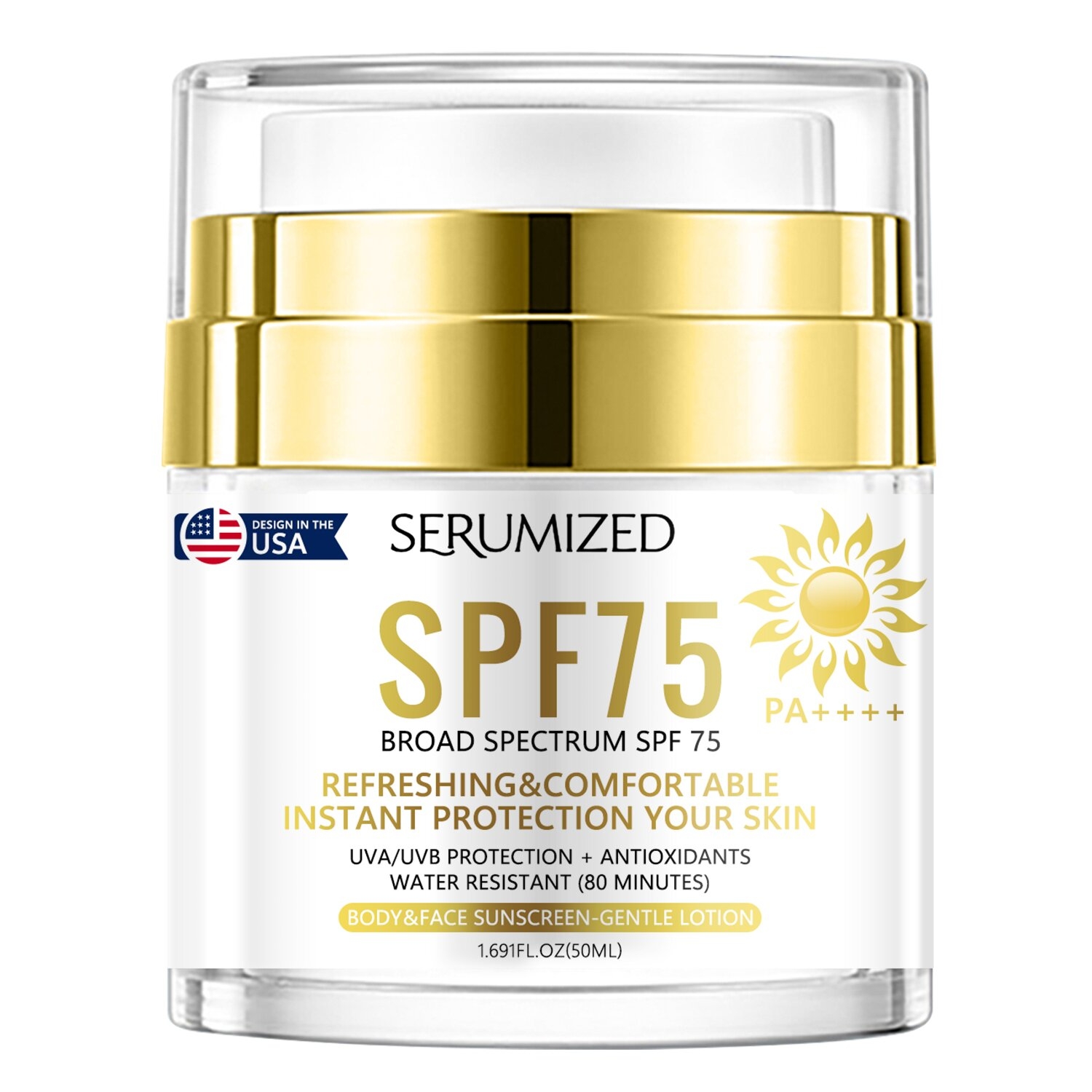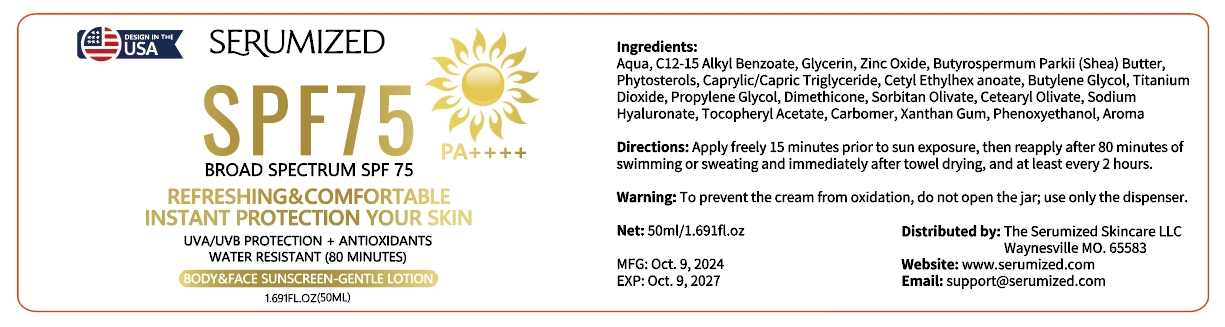 DRUG LABEL: SUNSCREEN
NDC: 84025-289 | Form: CREAM
Manufacturer: Guangzhou Yanxi Biotechnology Co., Ltd
Category: otc | Type: HUMAN OTC DRUG LABEL
Date: 20241220

ACTIVE INGREDIENTS: GLYCERIN 5 mg/50 mL; BUTYLENE GLYCOL 3 mg/50 mL
INACTIVE INGREDIENTS: WATER

DOSAGE AND ADMINISTRATION

Apply freely 15 minutes prior to sun exposure, then reapply after 80 minutes of swimming or sweating and immediately after towel drying, and at least every 2 hours.

WARNINGS

Keep out of children

INACTIVE INGREDIENT

Aqua

INDICATIONS AND USAGE

For daily skin care

Keep out of children

PURPOSE

Refreshing & comfortable instant protection your skin